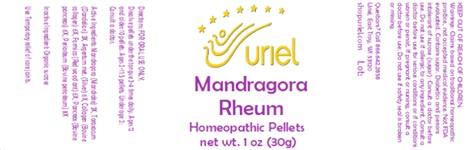 DRUG LABEL: Mandragora Rheum
NDC: 48951-7016 | Form: PELLET
Manufacturer: Uriel Pharmacy Inc.
Category: homeopathic | Type: HUMAN OTC DRUG LABEL
Date: 20231122

ACTIVE INGREDIENTS: MANDRAGORA OFFICINARUM ROOT 3 [hp_X]/1 1; TARAXACUM PALUSTRE ROOT 3 [hp_X]/1 1; SILVER 6 [hp_X]/1 1; BOVINE TYPE I COLLAGEN 6 [hp_X]/1 1; FORMICA RUFA 6 [hp_X]/1 1; SUS SCROFA PANCREAS 6 [hp_X]/1 1; BOS TAURUS BONE 8 [hp_X]/1 1
INACTIVE INGREDIENTS: SUCROSE

Mandragora Rheum

INDICATIONS AND USAGE

Directions: FOR ORAL USE ONLY.

DOSAGE AND ADMINISTRATION

Dissolve pellets under the tongue 3-4 times daily. Ages 12 and older: 10 pellets. Ages 2-11: 5 pellets. Under age 2: Consult a doctor.

ACTIVE INGREDIENT

Active Ingredients: Mandragora (Mandrake) 3X, Taraxacum (Dandelion) 3X, Argentum met. (Silver) 6X, Collagen (Bovine collagen) 6X, Formica (Red wood ant) 6X, Pancreas (Bovine pancreas) 6X, Periosteum (Bovine periosteum) 8X

Inactive Ingredients: Organic sucrose

PURPOSE

Use: Temporary relief of sore joints.

KEEP OUT OF REACH OF CHILDREN.

WARNINGS

Warnings: Claims based on traditional homeopathic practice, not accepted medical evidence. Not FDA evaluated. Contains sugar. Diabetics and persons intolerant of sucrose (sugar): Consult a doctor before use. Contains traces of lactose. Consult a doctor before use for serious conditions or if conditions worsen or persist. If pregnant or nursing, consult a doctor before use. Do not use if safety seal is broken or missing.

QUESTIONS

Questions? Call 866.642.2858 Uriel, East Troy, WI 53120 shopuriel.com